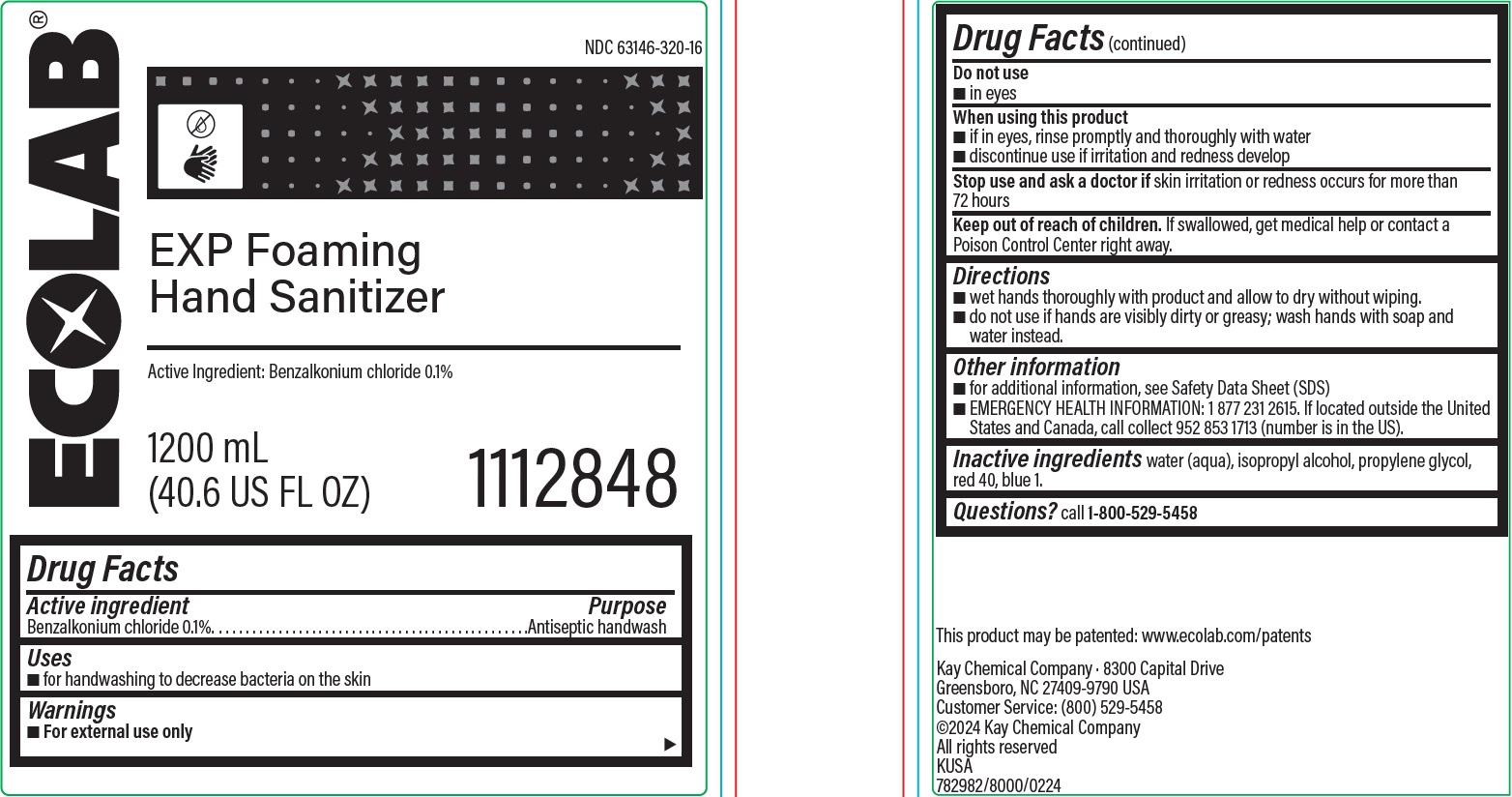 DRUG LABEL: EXP Foaming Hand Sanitizer
NDC: 47593-692 | Form: SOLUTION
Manufacturer: Ecolab Inc.
Category: otc | Type: HUMAN OTC DRUG LABEL
Date: 20251230

ACTIVE INGREDIENTS: BENZALKONIUM CHLORIDE 0.1 mg/100 mL
INACTIVE INGREDIENTS: WATER; ISOPROPYL ALCOHOL; PROPYLENE GLYCOL; FD&C RED NO. 40; FD&C BLUE NO. 1

Drug Facts

Active ingredient

Benzalkonium chloride 0.1%

Purpose

Antiseptic handwash

Uses

- for handwashing to decrease bacteria on the skin

Warnings

For external use only

Do not use

- in eyes

WHEN USING

- if in eyes, rinse promptly and thoroughly with water
- discontinue use if irritation and redness develop

Stop use and ask a doctor if skin irritation or redness occurs for more than 72 hours

Keep out of reach of children. If swallowed, get medical help or contact a Poison Control Center right away.

Direction

- wet hands thoroughly with product and allow to dry without wiping.
- do not use if hands are visibly dirty or greasy; wash hands with soap and water instead.

Other information

- for additional information, see Safety Data Sheet (SDS)
- EMERGENCY HEALTH INFORMATION: 1 877 231 2615. If located outside the United States and Canada, call collect 952 853 1713 (number is in the US).

INACTIVE INGREDIENT

Inactive ingredients water (aqua), isopropyl alcohol, propylene glycol, FD&C red 40, FD&C blue 1

Questions? call 1-800-529-5458

Principal display panel and representative label

ECOLAB

EXP Foaming Hand Sanitizer

Active Ingredient: Benzalkonium chloride 0.1%

1200 mL

(40.6 US FL OZ) 1112848

Kay Chemical Company · 8300 Capital Drive

Greensboro, NC 27409-9790 USA

Customer Service: (800) 529-5458

©2024 Kay Chemical Company

All rights reserved

KUSA

782982/8000/0224